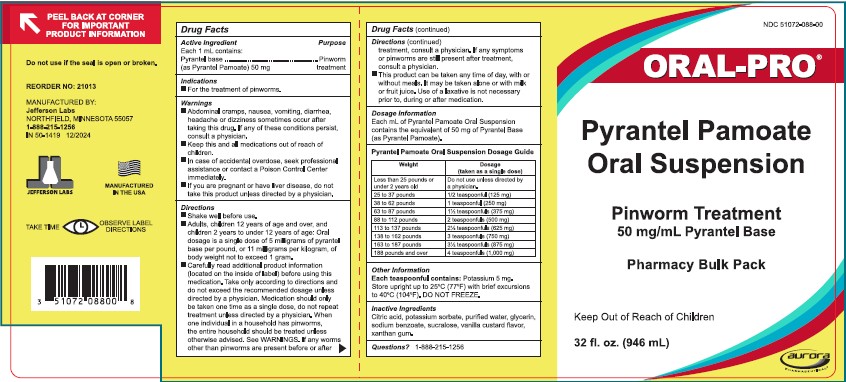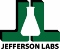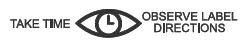 DRUG LABEL: Pyrantel Pamoate
NDC: 51072-088 | Form: SUSPENSION
Manufacturer: Jefferson Labs
Category: otc | Type: HUMAN OTC DRUG LABEL
Date: 20251219

ACTIVE INGREDIENTS: PYRANTEL PAMOATE 50 mg/1 mL
INACTIVE INGREDIENTS: CITRIC ACID MONOHYDRATE; POTASSIUM SORBATE; GLYCERIN; SODIUM BENZOATE; SUCRALOSE; XANTHAN GUM; WATER

ORAL-PRO®
Pyrantel Pamoate Oral Suspension
Pinworm Treatment

PURPOSE

50 mg/mL Pyrantel Base

Pharmacy Bulk Pack

Drug Facts

Active Ingredient | Purpose
Each 1 mL contains:
Pyrantel base | Pinworm
(as Pyrantel Pamoate) 50 mg | treatment

Indications

- For the treatment of pinworms.

Warnings

- Abdominal cramps, nausea, vomiting, diarrhea, headache or dizziness sometimes occur after taking this drug. If any of these conditions persist, consult a physician.
- Keep this and all medications out of reach of children.
- In case of accidental overdose, seek professional assistance or contact a Poison Control Center immediately.
- If you are pregnant or have liver disease, do not take this product unless directed by a physician.

Directions

- Shake well before use.
- Adults, children 12 years of age and over, and children 2 years to under 12 years of age: Oral dosage is a single dose of 5 milligrams of pyrantel base per pound, or 11 milligrams per kilogram, of body weight not to exceed 1 gram.
- Carefully read additional product information (located on the inside of label) before using this medication. Take only according to directions and do not exceed the recommended dosage unless directed by a physician. Medication should only be taken one time as a single dose, do not repeat treatment unless directed by a physician. When one individual in a household has pinworms, the entire household should be treated unless otherwise advised. See WARNINGS. If any worms other than pinworms are present before or after treatment, consult a physician. If any symptoms or pinworms are still present after treatment, consult a physician.
- This product can be taken any time of day, with or without meals. It may be taken alone or with milk or fruit juice. Use of a laxative is not necessary prior to, during or after medication.

Dosage Information

Each mL of Pyrantel Pamoate Oral Suspension contains the equivalent of 50 mg of Pyrantel Base (as Pyrantel Pamoate).

Pyrantel Pamoate Oral Suspension Dosage Guide

Weight | Dosage (taken as a single dose)
Less than 25 pounds or; under 2 years old | Do not use unless directed by; a physician
25 to 37 pounds | 1/2 teaspoonful (125 mg)
38 to 62 pounds | 1 teaspoonful (250 mg)
63 to 87 pounds | 1 1/2 teaspoonfuls (375 mg)
88 to 112 pounds | 2 teaspoonfuls (500 mg)
113 to 137 pounds | 2 1/2 teaspoonfuls (625 mg)
138 to 162 pounds | 3 teaspoonfuls (750 mg)
163 to 187 pounds | 3 1/2 teaspoonfuls (875 mg)
188 pounds and over | 4 teaspoonfuls (1,000 mg)

Other Information

Each teaspoonful contains: Potassium 5 mg.

STORAGE AND HANDLING

Store upright up to 25° C (77° F) with brief excursions 40° C (104° F). DO NOT FREEZE.

Inactive Ingredients

Citric acid, potassium sorbate, purified water, glycerin, sodium benzoate, sucralose, vanilla custard flavor, xanthan gum.

Questions? 1-888-215-1256

PEEL BACK AT CORNER FOR IMPORTANT PRODUCT INFORMATION

MANUFACTURED IN THE USA

Do not use if the seal is open or broken.

REORDER NO: 21013

Manufactured by:
Jefferson Labs
NORTHFIELD, MINNESOTA 55057
1-888-215-1256
IN 50-1419 12/2024

Keep Out of Reach of Children

PRINCIPAL DISPLAY PANEL - 946 mL Bottle Label

NDC 51072-088-00

ORAL-PRO®

Pyrantel Pamoate

Oral Suspension

Pinworm Treatment

50 mg/mL Pyrantel Base

Pharmacy Bulk Pack

Keep Out of Reach of Children

32 fl. oz. (946 mL)